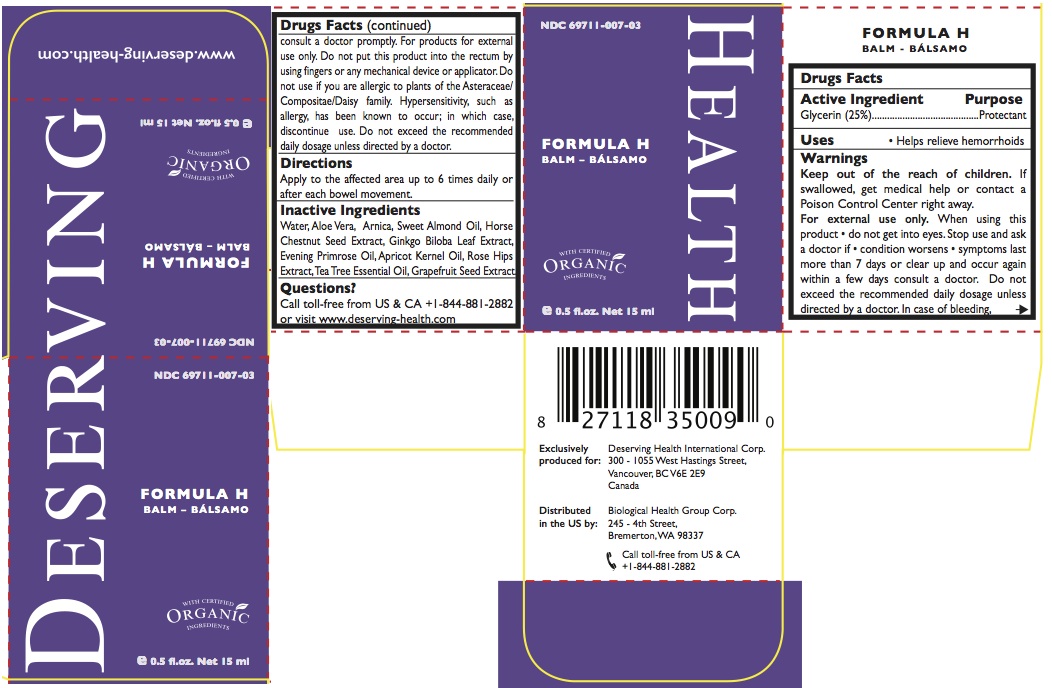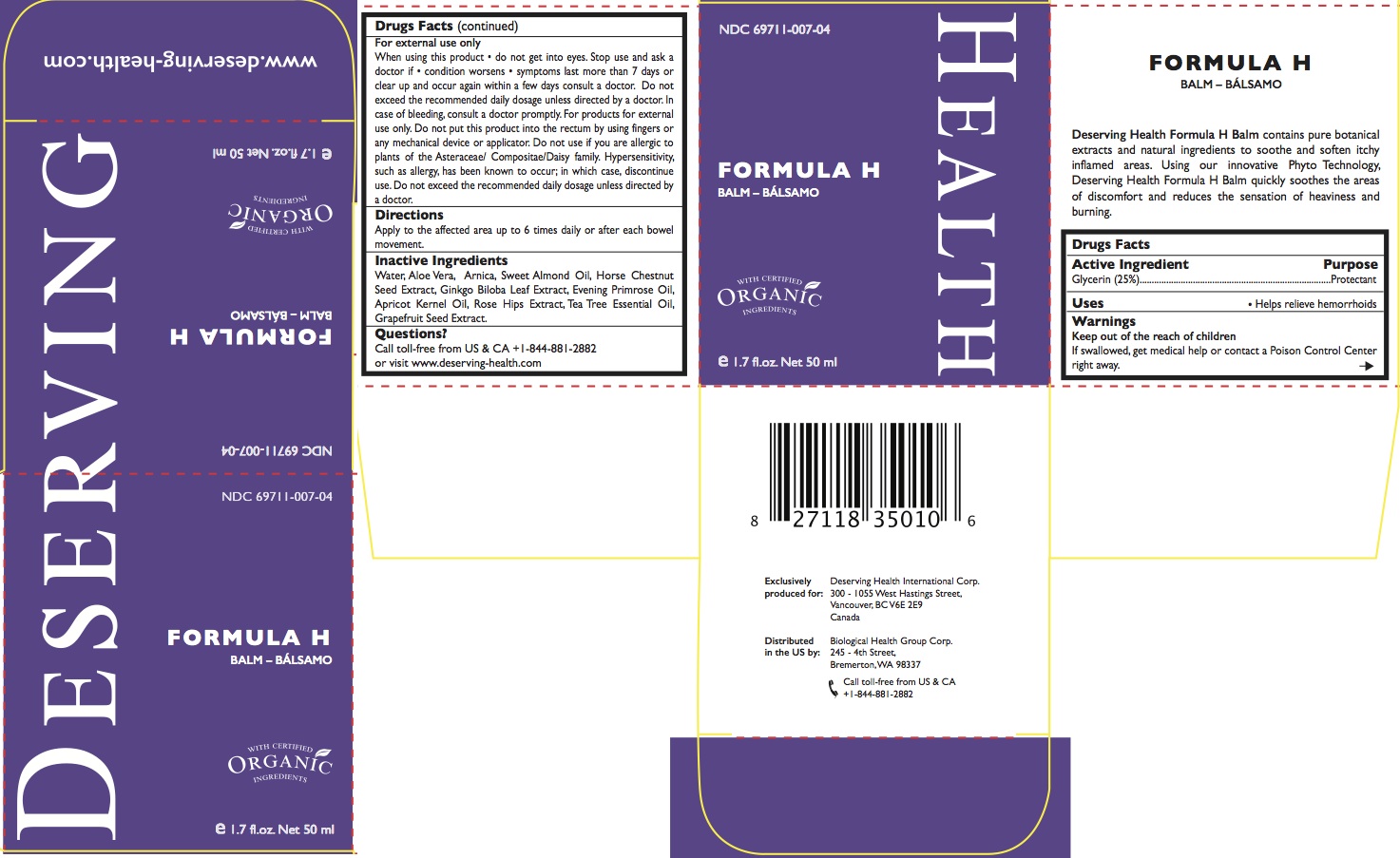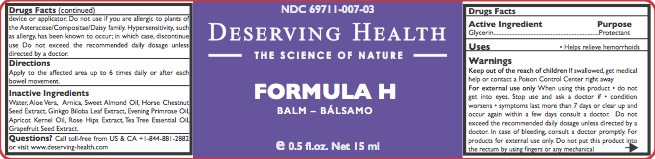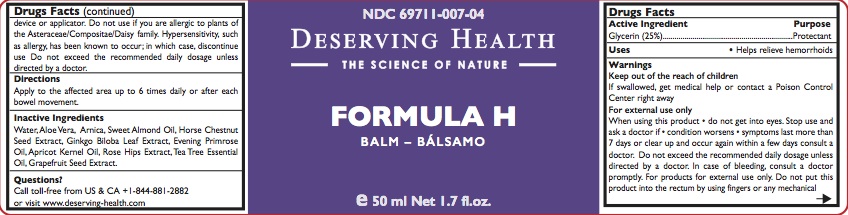 DRUG LABEL: FORMULA H
NDC: 69711-007 | Form: CREAM
Manufacturer: Biological Health Group Corporation
Category: otc | Type: HUMAN OTC DRUG LABEL
Date: 20150619

ACTIVE INGREDIENTS: GLYCERIN 25 g/100 mL
INACTIVE INGREDIENTS: ALOE VERA LEAF; ARNICA MONTANA; ALMOND OIL; HORSE CHESTNUT; GINKGO; EVENING PRIMROSE OIL; APRICOT KERNEL OIL; ROSA CANINA FRUIT OIL; TEA TREE OIL; CITRUS PARADISI SEED; WATER

FORMULA H
BALM – BÁLSAMO

ACTIVE INGREDIENT

Glycerin 25%

PURPOSE

Protectant

USES

- Helps relieve hemorrhoids

Keep out of the reach of children. If swallowed, get medical help or contact a Poison Control Center right away.

DIRECTIONS

Apply to the affected area up to 6 times daily or after each bowel movement.

INACTIVE INGREDIENTS

Water, Aloe Vera, Arnica, Sweet Almond Oil, Horse Chestnut Seed Extract, Ginkgo Biloba Leaf Extract, Evening Primrose Oil, Apricot Kernel Oil, Rose Hips Extract, Tea Tree Essential Oil, Grapefruit Seed Extract

Questions?

Call toll-free from US & CA +1-844-881-2882 or visit www.deserving-health.com

WARNINGS

For external use only.

When using this product • do not get into eyes.

Stop use and ask a doctor if

- condition worsens
- symptoms last more than 7 days, or clear up and occur again within a few days, consult a doctor.
- In case of bleeding, consult a doctor promptly.

When using

- Do not exceed the recommended daily dosage unless directed by a doctor. Do not put this product into the rectum by using fingers or any mechanical device or applicator.

Do not use if you are allergic to plants of the Asteraceae/ Compositae/Daisy family. Hypersensitivity, such as allergy, has been known to occur; in which case, discontinue use.